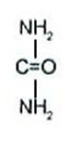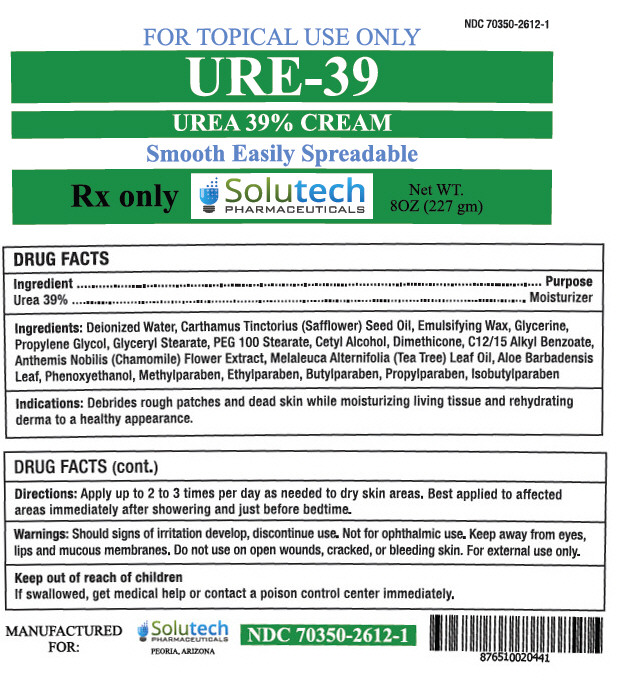 DRUG LABEL: URE-39
NDC: 70350-2612 | Form: CREAM
Manufacturer: SOLUTECH PHARMACEUTICALS LLC
Category: prescription | Type: HUMAN PRESCRIPTION DRUG LABEL
Date: 20180314

ACTIVE INGREDIENTS: UREA 390 mg/1 g
INACTIVE INGREDIENTS: WATER; SAFFLOWER OIL; GLYCERIN; PROPYLENE GLYCOL; GLYCERYL MONOSTEARATE; PEG-100 STEARATE; CETYL ALCOHOL; DIMETHICONE; ALKYL (C12-15) BENZOATE; CHAMAEMELUM NOBILE FLOWER; TEA TREE OIL; ALOE VERA LEAF; PHENOXYETHANOL; METHYLPARABEN; ETHYLPARABEN; BUTYLPARABEN; PROPYLPARABEN; ISOBUTYLPARABEN

URE-39
(Urea 39% Cream)

Rx only

For external use only.

Not for ophthalmic use.

URE-39 Description

URE-39 Cream is a potent keratolytic emollient which is a gentle, yet potent, tissue softener for skin and/or nails.

Each gram of URE-39 Cream contains:

ACTIVE: 39% Urea in a cream base of:

INACTIVES: Deionized Water, Carthamus Tinctorius (Safflower) Seed Oil, Emulsifying Wax, Glycerine, Propylene Glycol, Glyceryl Stearate, PEG 100 Stearate, Cetyl Alcohol, Dimethicone, C12/15 Alkyl Benzoate, Anthemis Nobilis (Chamomile) Flower Extract, Melaleuca Alternifolia (Tea Tree) Leaf Oil, Aloe Barbadensis Leaf, Phenoxyethanol, Methylparaben, Ethylparaben, Butylparaben, Propylparaben, and Isobutylparaben.

CHEMISTRY

Urea is a diamide of carbonic acid with the following chemical structure:

URE-39 - Clinical Pharmacology

Urea gently dissolves the intercellular matrix which results in loosening the horny layer of skin and shedding scaly skin at regular intervals, thereby softening hyperkeratotic areas. Urea also hydrates and gently dissolves the intercellular matrix of the nail plate, which can result in the softening and eventual debridement of the nail plate.

PHARMACOKINETICS

The mechanism of action of topically applied Urea is not yet known.

INDICATIONS AND USES

For debridement and promotion of normal healing of hyperkeratotic surface lesions, particularly where healing is retarded by local infection, necrotic tissue, fibrinous or prurient debris or eschar. Urea is useful for the treatment of hyperkeratotic conditions such as dry, rough skin, dermatitis, psoriasis, xerosis, ichthyosis, eczema, keratosis, keratoderma, corns and calluses, as well as damaged, ingrown and devitalized nails.

Contraindications

URE-39 Cream is contraindicated in patients with known hypersensitivity to any of the listed ingredients.

Warnings

For external use only. Avoid contact with eyes, lips or mucous membranes. Do not use on areas of broken skin.

Precautions

Stop use and ask a doctor if redness or irritation develops. After applying this medication, wash hands and unaffected areas thoroughly. If swallowed, get medical help or contact Poison Control Center right away. KEEP THIS AND ALL MEDICATION OUT OF THE REACH OF CHILDREN.

PREGNANCY

Pregnancy Category B

Animal reproduction studies have revealed no evidence of harm to the fetus, however, there are no adequate and well-controlled studies in pregnant women. Because animal reproduction studies are not always predictive of human response, URE-39 Cream should be given to a pregnant woman only if clearly needed.

NURSING MOTHERS

It is not known whether or not this drug is secreted in human milk. Because many drugs are secreted in human milk, caution should be exercised when URE-39 Cream is administered to a nursing woman.

Adverse Reactions

Transient stinging, burning, itching or irritation may occur and normally disappear on discontinuing the medication.

URE-39 - Dosage and Administration

Apply URE-39 Cream to affected skin two to three times per day as needed or as directed by a physician. Rub in until completely absorbed. Apply to diseased or damaged nail tissue two to three times per day or as directed by a physician. Best applied to affected areas immediately after showering and just before bedtime.

How is URE-39 Supplied

URE-39 (39% Urea Cream) is supplied in:

8oz (227gm) Jar | NDC: 70350-2612-1

STORAGE AND HANDLING

Store at 25°C (77°F); excursions permitted to 15°C - 30°C (59° - 86°F). Protect from freezing. [See USP Controlled Room Temperature.]

Manufactured for:
Solutech Pharmaceuticals LLC
Peoria, AZ 85345

Rx only

PRINCIPAL DISPLAY PANEL - 227 gm Jar Label

NDC 70350-2612-1

FOR TOPICAL USE ONLY

URE-39
UREA 39% CREAM

Smooth Easily Spreadable

Rx only

Solutech
PHARMACEUTICALS

Net WT.
8OZ (227 gm)